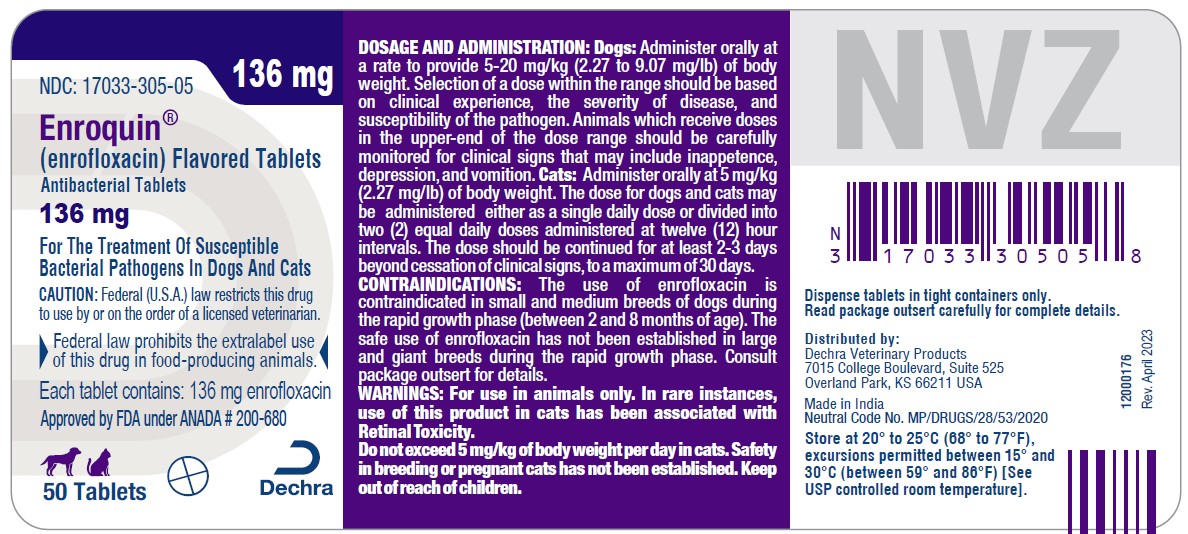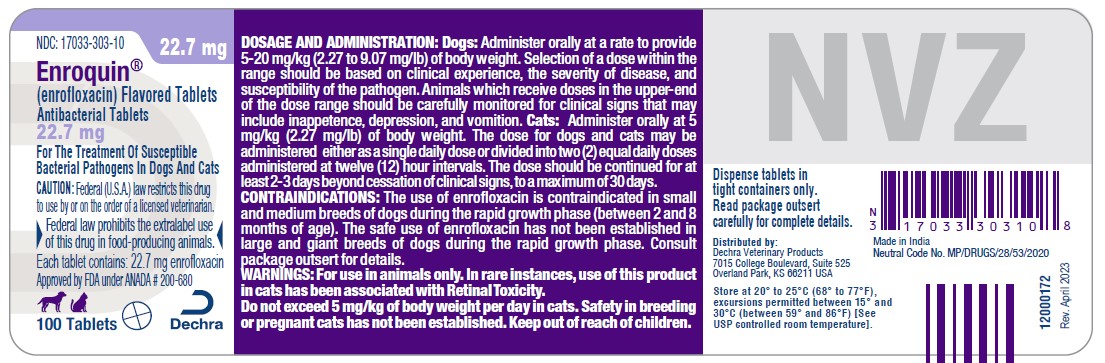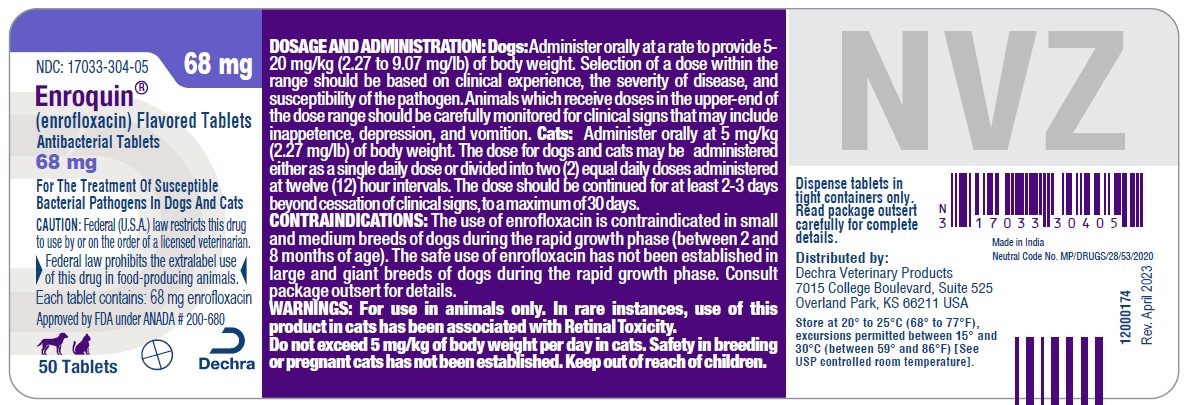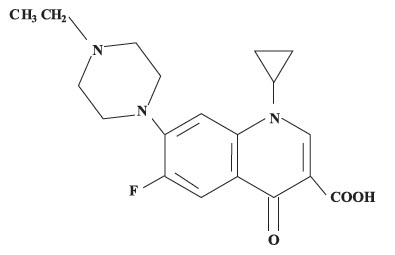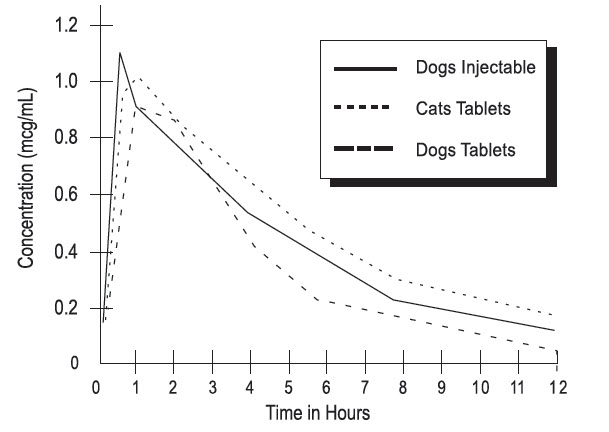 DRUG LABEL: Enroquin Flavored
NDC: 17033-303 | Form: TABLET
Manufacturer: Dechra Veterinary Products, LLC
Category: animal | Type: PRESCRIPTION ANIMAL DRUG LABEL
Date: 20260226

ACTIVE INGREDIENTS: Enrofloxacin 22.7 mg/1 1

Enroquin®
(enrofloxacin)
Flavored Tablets

Antibacterial Tablets for Dogs and Cats

SAFE HANDLING WARNING

CAUTION:

Federal (U.S.A.) law restricts this drug to use by or on the order of a licensed veterinarian.

▶ Federal law prohibits the extralabel use of this drug in food-producing animals. ◀

DESCRIPTION:

Enrofloxacin is a synthetic chemotherapeutic agent from the class of the quinolone carboxylic acid derivatives. It has antibacterial activity against a broad spectrum of Gram negative and Gram positive bacteria (See Tables Iand II). It is rapidly absorbed from the digestive tract, penetrating into all measured body tissues and fluids (SeeTable III). Tablets are available in three sizes (22.7, 68.0 and 136.0 mg enrofloxacin).

CHEMICAL NOMENCLATURE AND STRUCTURAL FORMULA:

1-cyclopropyl-7-(4-ethyl-1-piperazinyl)-6-fluoro-1,4-dihydro-4-oxo-3-quinolinecarboxylic acid.

MECHANISM OF ACTION

ACTIONS:

Microbiology:

Quinolone carboxylic acid derivatives are classified as DNA gyrase inhibitors. The mechanism of action of these compounds is very complex and not yet fully understood. The site of action is bacterial gyrase, a synthesis promoting enzyme. The effect on Escherichia coli is the inhibition of DNA synthesis through prevention of DNA supercoiling. Among other things, such compounds lead to the cessation of cell respiration and division. They may also interrupt bacterial membrane integrity.^1

Enrofloxacin is bactericidal, with activity against both Gram negative and Gram positive bacteria. The minimum inhibitory concentrations (MICs) were determined for a series of 39 isolates representing 9 genera of bacteria from natural infections in dogs and cats, selected principally because of resistance to one or more of the following antibiotics: ampicillin, cephalothin, colistin, chloramphenicol, erythromycin, gentamicin, kanamycin, penicillin, streptomycin, tetracycline, triple sulfa and sulfa/trimethoprim. The MIC values forenrofloxacin against these isolates are presented in Table I. Most strains of these organisms were found to be susceptible to enrofloxacin in vitro but the clinical significance has not been determined for some of the isolates.

The susceptibility of organisms to enrofloxacin should be determined using enrofloxacin 5 mcg disks. Specimens for susceptibility testing should be collected prior to the initiation ofenrofloxacin therapy.

TABLE I — MIC Values for Enrofloxacin Against Canine and Feline Pathogens (Diagnostic laboratory isolates, 1984)
Organisms | Isolates | MIC Range (mcg/mL)
Bacteroides spp. | 2 | 2
Bordetella bronchiseptica | 3 | 0.125-0.5
Brucella canis | 2 | 0.125-0.25
Clostridium perfringens | 1 | 0.5
Escherichia coli | 5 [Includes feline isolates.] | ≤ 0.016-0.031
Klebsiella spp. | 11 | 0.031-0.5
Proteus mirabilis | 6 | 0.062-0.125
Pseudomonas aeruginosa | 4 | 0.5-8
Staphylococcus spp. | 5 | 0.125

The inhibitory activity on 120 isolates of seven canine urinary pathogens was also investigated and is listed in Table II.

TABLE II — MIC Values for Enrofloxacin Against Canine Urinary Pathogens (Diagnostic laboratory isolates, 1985)
Organisms | Isolates | MIC Range (mcg/mL)
E. coli | 30 | 0.06-2.0
P. mirabilis | 20 | 0.125-2.0
K. pneumoniae | 20 | 0.06-0.5
P. aeruginosa | 10 | 1.0-8.0
Enterobacter spp. | 10 | 0.06-1.0
Staph. (coag. +) | 20 | 0.125-0.5
Strep. (alpha hemol.) | 10 | 0.5-8.0

Distribution in the Body: Enrofloxacin penetrates into all canine and feline tissues and body fluids. Concentrations of drug equal to or greater than the MIC for many pathogens (See Tables I, II and III) are reached in most tissues by two hours after dosing at 2.5 mg/kg and are maintained for 8-12 hours after dosing. Particularly high levels ofenrofloxacin are found in urine.Asummary of the body fluid/tissue drug levels at 2 to 12 hours after dosing at 2.5 mg/kg is given in Table III.

TABLE III — Body Fluid/Tissue distribution of Enrofloxacin in Dogs and Cats
Single Oral Dose= 2.5 mg/kg (1.13 mg/lb)
 | Post-treatment Enrofloxacin Levels
 | Canine (n = 2) |  | Feline (n = 4)
Body Fluids (mcg/mL) | 2 Hr. | 8 Hr. | 2 Hr. | 12 Hr.
Bile | – | – | 2.13 | 1.97
Cerebrospinal Fluid | – | – | 0.37 | 0.10
Urine | 43.05 | 55.35 | 12.81 | 26.41
Eye Fluids | 0.53 | 0.66 | 0.45 | 0.65
Whole Blood | 1.01 | 0.36 | – | –
Plasma | 0.67 | 0.33 | – | –
Serum | – | – | 0.48 | 0.18
Tissues (mcg/g) Hematopoietic System
Liver | 3.02 | 1.36 | 1.84 | 0.37
Spleen | 1.45 | 0.85 | 1.33 | 0.52
Bone Marrow | 2.10 | 1.22 | 1.68 | 0.64
Lymph Node | 1.32 | 0.91 | 0.49 | 0.21
Urogenital System
Kidney | 1.87 | 0.99 | 1.43 | 0.37
Bladder Wall | 1.36 | 0.98 | 1.16 | 0.55
Testes | 1.36 | 1.10 | 1.01 | 0.28
Prostate | 1.36 | 2.20 | 1.88 | 0.55
Ovaries | – | – | 0.78 | 0.56
Uterine Wall | 1.59 | 0.29 | 0.81 | 1.05
Gastrointestinal and Cardiopulmonary Systems
Lung | 1.34 | 0.82 | 0.91 | 0.33
Heart | 1.88 | 0.78 | 0.84 | 0.32
Stomach | 3.24 | 2.16 | 3.26 | 0.27
Small Intestine | 2.10 | 1.11 | 2.72 | 0.40
Large Intestine | – | – | 0.94 | 1.10
Other
Fat | 0.52 | 0.40 | 0.24 | 0.11
Skin | 0.66 | 0.48 | 0.46 | 0.17
Muscle | 1.62 | 0.77 | 0.53 | 0.29
Brain | 0.25 | 0.24 | 0.22 | 0.12
Mammary Gland | 0.45 | 0.21 | 0.36 | 0.30
Feces | 1.65 | 9.97 | 0.37 | 4.18

Pharmacokinetics:

In dogs, the absorption and elimination characteristics of the oral formulation are linear (plasma concentrations increase proportionally with dose) when enrofloxacin is administered at up to 11.5 mg/kg, twice daily.^2Approximately 80% of the orally administered dose enters the systemic circulation unchanged. The eliminating organs, based on the drug's body clearance time, can readily remove the drug with no indication that the eliminating mechanisms are saturated. The primary route of excretion is via the urine. The absorption and elimination characteristics beyond this point are unknown. In cats, no oral absorption information is available at other than 2.5 mg/kg, administered orally as a single dose. Saturable absorption and/or elimination processes may occur at greater doses. When saturation of the absorption process occurs, the plasma concentration of the active moiety will be less than predicted, based on the concept of dose proportionality.

Following an oral dose in dogs of 2.5 mg/kg (1.13 mg/lb), enrofloxacin reached 50% of its maximum serum concentration in 15 minutes and peak serum level was reached in one hour. The elimination half-life in dogs is approximately 2½ - 3 hours at that dose, while in cats it is greater than 4 hours. In a study comparing dogs and cats, the peak concentration and the time to peak concentration were not different.

A graph indicating the mean serum levels following a dose of 2.5 mg/kg (1.13 mg/lb) in dogs (oral and intramuscular) and cats (oral) is shown in Figure 1.

Figure 1 - Serum Concentrations of Enrofloxacin Following a Single Oral or Intramuscular Dose at 2.5 mg/kg in Dogs and a Single Oral Dose at 2.5 mg/kg in Cats.

Breakpoint: Based on pharmacokinetic studies of enrofloxacin in dogs and cats after a single oral administration of 2.5 mg enrofloxacin/kg BW (i.e. half of the lowest-end single daily dose range for dogs and half the single daily dose for cats) and the data listed in Tables I and II, the following breakpoints are recommended for canine and feline isolates.

Zone Diameter (mm) | MIC (μg/mL) | Interpretation
≥ 21 | ≤ 0.5 | Susceptible (S)
18 - 20 | 1 | Intermediate (I)
≤ 17 | ≥ 2 | Resistant (R)

A report of "Susceptible" indicates that the pathogen is likely to be inhibited by generally achievable plasma levels. A report of "Intermediate" is a technical buffer and isolates falling into this category should be retested. Alternatively the organism may be successfully treated if the infection is in a body site where drug is physiologically concentrated. A report of "Resistant" indicates that the achievable drug concentrations are unlikely to be inhibitory and other therapy should be selected.

Standardized procedures require the use of laboratory control organisms for both standardized disk diffusion assays and standardized dilution assays. The 5 µg enrofloxacin disk should give the following zone diameters and enrofloxacin powder should provide the following MIC values for reference strains.

QC strain | MIC (μg/mL) | Zone Diameter (mm)
E. coli ATCC 25922 | 0.008 - 0.03 | 32 - 40
P. aeruginosa ATCC 27853 | 1 - 4 | 15 - 19
S. aureus ATCC 25923 |  | 27 - 31
S. aureus ATCC 29213 | 0.03 - 0.12

INDICATIONS:

Enroquin (enrofloxacin) Flavored Tablets are indicated for the management of diseases associated with bacteria susceptible to enrofloxacin. Enroquin Flavored Tablets are indicated for use in dogs and cats.

EFFICACY CONFIRMATION:

Dogs: Clinical efficacy was established in dermal infections (wounds and abscesses) associated with susceptible strains of Escherichia coli, Klebsiella pneumoniae, Proteus mirabilis, and Staphylococcus intermedius; respiratory infections (pneumonia, tonsillitis, rhinitis) associated with susceptible strains ofEscherichia coli and Staphylococcus aureus; and urinary cystitis associated with susceptible strains ofEscherichia coli, Proteus mirabilis, and Staphylococcus aureus.

Cats: Clinical efficacy was established in denmal infections (wounds and abscesses) associated with susceptible strains of Pasteurella multocida, Staphylococcus aureus, and Staphylococcus epidermidis.

CONTRAINDICATIONS:

Enrofloxacin is contraindicated in dogs and cats known to be hypersensitive to quinolones.

Dogs: Based on the studies discussed under the section on Animal Safety Summary, the use of enrofloxacin is contraindicated in small and medium breeds of dogs during the rapid growth phase (between 2 and 8 months of age). The safe use of enrofloxacin has not been established in large and giant breeds during the rapid growth phase. Large breeds may be in this phase for up to one year of age and the giant breeds for up to 18 months. In clinical field trials utilizing a daily oral dose of 5.0 mg/kg, there were no reports of lameness or joint problems in any breed. However, controlled studies with histological examination of the articular cartilage have not been conducted in the large or giant breeds.

ADVERSE REACTIONS:

Dogs: Two of the 270 (0.7%) dogs treated with enrofloxacin at 5.0 mg/kg per day in the clinical field studies exhibited side effects, which were apparently drug-related. These two cases ofvomition were self-limiting.

Post-Approval Experience: The following adverse experiences, although rare, are based on voluntary post-approval adverse drug experience reporting. The categories of reactions are listed in decreasing order of frequency by body system.

Gastrointestinal: anorexia, diarrhea, vomiting, elevated liver enzymes

Neurologic: ataxia, seizures

Behavioral: depression, lethargy, nervousness

Cats: No drug-related side effects were reported in 124 cats treated with enrofloxacin at 5.0 mg/kg per day for 10 days in clinical field studies.

Post-Approval Experience: The following adverse experiences, although rare, are based on voluntary post-approval adverse drug experience reporting. The categories of reactions are listed in decreasing order of frequency by body system.

Ocular: Mydriasis, retinal degeneration (retinal atrophy, attenuated retinal vessels, and hyperreflective tapeta have been reported), loss of vision. Mydriasis may be an indication of impending or existing retinal changes.

Gastrointestinal: vomiting, anorexia, elevated liver enzymes, diarrhea

Neurologic: ataxia, seizures

Behavioral: depression, lethargy, vocalization, aggression

To report suspected adverse drug events, for technical assistance or to obtain a copy of the Safety Data Sheet, contact Dechra at (866) 933-2472. For additional information about adverse drug experience reporting for animal drugs, contact FDA at 1-888-FDA-VETS or http://www.fda.gov/reportanimalae.

ANIMAL SAFETY SUMMARY:

Dogs: Adult dogs receiving enrofloxacin orally at a daily dosage rate of 52 mg/kg for 13 weeks had only isolated incidences of vomition and inappetence. Adult dogs receiving the tablet formulalion for 30 consecutive days at a daily treatment of 25 mg/kg did not exhibit significant clinical signs nor were there effects upon the clinical chemistry, hematological or histological parameters. Daily doses of 125 mg/kg for up to 11 days induced vomition, inappetence, depression, difficult locomotion and death while adult dogs receiving 50 mg/kg/day for 14 days had clinical signs ofvomition and inappetence.

Adult dogs dosed intramuscularly for three treatments at 12.5 mg/kg followed by 57 oral treatments at 12.5 mg/kg, all at 12 hour intervals, did not exhibit either significant clinical signs or effects upon the clinical chemistry, hematological or histological parameters.

Oral treatment of 15 to 28 week old growing puppies with daily dosage rates of 25 mg/kg has induced abnormal carriage of the carpal joint and weakness in the hindquarters. Significant improvement of clinical signs is observed following drug withdrawal. Microscopic studies have identified lesions of the articular cartilage following 30 day treatments at either 5, 15 or 25 mg/kg in this age group. Clinical signs of difficult ambulation or associated cartilage lesions have not been observed in 29 to 34 week old puppies following daily treatments of 25 mg/kg for 30 consecutive days nor in 2 week old puppies with the same treatment schedule.

Tests indicated no effect on circulating microfilariae or adult heartworms (Dirofilaria immitis) when dogs were treated ala daily dosage rate of 15 mg/kg for 30 days. No effect on cholinesterase values was observed.

No adverse effects were observed on reproductive parameters when male dogs received 10 consecutive daily treatments of 15 mg/kg/day at 3 intervals (90, 45 and 14 days) prior to breeding or when female dogs received 10 consecutive daily treatments of 15 mg/kg/day at 4 intervals: between 30 and 0 days prior to breeding, early pregnancy (between 10th & 30th days), late pregnancy (between 40th & 60th days), and during lactation (the first 28 days).

Cats: Cats in age ranges of 3 to 4 months and 7 to 10 months received daily treatments of 25 mg/kg for 30 consecutive days with no adverse effects upon the clinical chemistry, hematolo9ical or histological parameters. In cats 7-10 months of age treated daily for 30 consecutive days, 2 of 4 receiving 5 mg/kg, 3 of 4 receiving 15 mg/kg, 2 of 4 receiving 25 mg/kg and 1 of 4 nontreated controls experienced occasional vomition. Five to 7 month old cats had no side effects with daily treatments of 15 mg/kg for 30 days, but 2 of 4 animals had articular cartilage lesions when administered 25 mg/kg per day for 30 days.

Doses of 125 mg/kg for 5 consecutive days to adult cats induced vomition, depression, incoordination and death while those receiving 50 mg/kg for 6 days had clinical signs of vomition, inappetence, incoordination and convulsions, but they returned to normal.

Enrofloxacin was administered to thirty-two (8 per group), six- to eight-month-old cats at doses of 0, 5, 20, and 50 mg/kg of body weight once a day for 21 consecutive days. There were no adverse effects observed in cats that received 5 mg/kg body weight of enrofloxacin. The administration of enrofloxacin at 20 mg/kg body weight or greater caused salivation, vomition, and depression. Additionally, dosing at 20 mg/kg body weight or greater resulted in mild to severe fundic lesions on ophthalmologic examination (change in color of the fund us, central or generalized retinal degeneration), abnormal electroretinograms (including blindness), and diffuse light microscopic changes in the retina.

DRUG INTERACTIONS:

Compounds that contain metal cations (e.g., aluminum, calcium, iron, magnesium) may reduce the absorption of some quinolone-class drugs from the intestinal tract. Concomitant therapy with other drugs that are metabolized in the liver may reduce the clearance rates of the quinoloneand the other drug.

Dogs: Enrofloxacin has been administered to dogs at a daily dosage rate of 10 mg/kg concurrently with a wide variety of other health products including anthelmintics (praziquantel, febantel, sodium disophenol), insecticides (fenthion, pyrethrins), heartworm preventatives (diethylcarbamazine) and other antibiotics (ampicillin, gentamicin sulfate, penicillin, dihydrostreptomycin). No incompatibilities with other drugs are known at this lime.

Cats: Enrofloxacin was administered at a daily dosage rate of 5 mg/kg concurrently with anthelmintics (praziquantel, febantel), an insecticide (propoxur) and another antibacterial (ampicillin). No incompatibilities with other drugs are known at this time.

WARNINGS:

For use in animals only. In rare instances, use of this product in cats has been associated with Retinal Toxicity. Do not exceed 5 mg/kg of body weight per day in cats. Safety in breeding or pregnant cats has not been established. Keep out of reach of children.

Avoid contact with eyes. In case of contact, immediately flush eyes with copious amounts of water for 15 minutes. In case of dermal contact, wash skin with soap and water.

Consult a physician if irritation persists following ocular or dermal exposure. Individuals with a history of hypersensitivity to quinolones should avoid this product. In humans, there is a risk of user photosensitization within a few hours after excessive exposure to quinolones. If excessive accidental exposure occurs, avoid direct sunlight.

For customer service or to obtain product information, including Safety Data Sheet, call (866)933-2472.

Keep Enroquin (enrofloxacin) Flavored Tablets in a secure location out of reach of dogs, cats, and other animals lo prevent accidental ingestion or overdose.

PRECAUTIONS:

Quinolone-class drugs should be used with caution in animals with known or suspected Central Nervous System (CNS) disorders. In such animals, quinolones have, in rare instances, been associated with CNS stimulation which may lead to convulsive seizures.

Quinolone-class drugs have been associated with cartilage erosions in weight-bearing joints and other forms of arthropathy in immature animals of various species.

The use of fluoroquinolones in cats has been reported to adversely affect the retina. Such products should be used with caution in cats.

DOSAGE AND ADMINISTRATION:

Dogs: Administer orally at a rate to provide 5-20 mg/kg (2.27 to 9.07 mg/lb) of body weight. Selection of a dose within the range should be based on clinical experience, the severity of disease, and susceptibility of the pathogen. Animals which receive doses in the upper-end of the dose range should be carefully monitored for clinical signs that may include inappetence, depression, and vomition. If dogs do not consume Enroquin Flavored Tablets willingly when offered by hand, then alternatively the tablet(s) may be offered in the food or hand- administered (pilled) as with other oral tablet medications.

Weight of Dog | Once Daily Dosing Chart
 | 5.0 mg/kg | 10.0 mg/kg | 15.0 mg/kg | 20.0 mg/kg
9.1 kg (20 lb) | 2 × 22.7 mg tablets | 1 × 22.7 mg plus 1 × 68 mg tablets | 1 × 136 mg tablet | 1 × 136 mg plus 2 × 22.7 mg tablets
27.2 kg (60 lb) | 1 × 136 mg tablets | 2 × 136 mg tablets | 3 × 136 mg tablets | 4 × 136 mg tablets

All tablet sizes are double scored for accurate dosing.

Cats: Administer orally at 5 mg/kg (2.27 mg/lb) of bodyweight. The dose for dogs and cats may be administered either as a single daily dose or divided into two (2) equal daily doses administered at twelve (12) hour intervals. The dose should be continued for at least 2-3 days beyond cessation of clinical signs, to a maximum of 30 days. In cats, Enroquin Flavored Tablets should be pilled. After administration, watch the animal closely to be certain the entire dose has been consumed.

Weight of Cat |  | Once Daily Dosing Chart (5 mg/kg/day)
5 lb (2.27 kg) |  | 1/2 × 22.7 mg tablet
10 lb (4.5 kg) |  | 1 × 22.7 mg tablet
15 lb (6.8 kg) |  | 1 and 1/2 × 22.7 mg tablets or 1/2 × 68 mg tablet

All tablet sizes are double scored for accurate dosing.

Dogs & Cats: The duration of treatment should be selected based on clinical evidence.

Generally, administration of Enroquin Flavored Tablets should continue for at least 2-3 days beyond cessation of clinical signs. For severe and/or complicated infections, more prolonged therapy, up to 30 days, may be required. If no improvement is seen within five days, the diagnosis should be re-evaluated and a different course of therapy considered.

The lower limit of the dose range in dogs and the daily dose for cats was based on efficacy studies in dogs and cats where enrofloxacin was administered at 2.5 mg/kg twice daily. Target animal safety and toxicology were used to establish the upper limit ofthe dose range for dogs and treatment duration for dogs and cats.

STORAGE:

Dispense tablets in tight containers only.

Store at 20° to 25°C (68° to 77°F), excursions permitted between 15° and 30°C (between 59° and 86°F) [see USP Controlled Room Temperature].

HOW SUPPLIED:

NDC Number | Enroquin Flavored Tablets Tablet Size | Tablets/Bottle
17033-303-10 | 22.7 mg | 100 Double Scored
17033-303-50 | 22.7 mg | 500 Double Scored
17033-304-05 | 68.0 mg | 50 Double Scored
17033-304-25 | 68.0 mg | 250 Double Scored
17033-305-05 | 136.0 mg | 50 Double Scored
17033-305-20 | 136.0 mg | 200 Double Scored

REFERENCES:

1. Doughherty, T.J., & Saukkonen, J.J. (1985). Membrane permeability changes associated with DNA gyrase inhibitors in Escherichia Coli. Antimicrob Agents Chemother, 28 (2), 200-206.

2. Walker, R.D., Stein, G.E., Hauptmam, J.G., McDonald, K.H. (1992). Pharmacokinetic evaluation of enrofloxacin administered orally to healthy dogs. Am J Vet Res, 53 (12): 2315-2319.

Approved by FDA under ANADA # 200-680

Distributed by:
Dechra Veterinary Products
7015 College Boulevard, Suite 525
Overland Park, KS 66211 USA

Made in India

Neutral Code No. MP/DRUGS/28/53/2020

Enroquin® is a registered trademark of Dechra Veterinary Products, LLC.

Rev. April 2023

12000203

PRINCIPAL DISPLAY PANEL - 22.7 mg Tablet Bottle Label

NDC: 17033-303-10

22.7 mg

Enroquin®

(enrofloxacin) Flavored Tablets
Antibacterial Tablets

22.7 mg

For The Treatment Of Susceptible
Bacterial Pathogens In Dogs And Cats

CAUTION: Federal (U.S.A.) law restricts this drug
to use by or on the order of a licensed veterinarian.

Federal law prohibits the extralabel use
of this drug in food-producing animals.

Each tablet contains: 22.7 mg enrofloxacin
Approved by FDA under ANADA # 200-680

100 Tablets

Dechra

PRINCIPAL DISPLAY PANEL - 68 mg Tablet Bottle Label

NDC: 17033-304-05

68 mg

Enroquin®

(enrofloxacin) Flavored Tablets
Antibacterial Tablets

68 mg

For The Treatment Of Susceptible
Bacterial Pathogens In Dogs And Cats

CAUTION: Federal (U.S.A.) law restricts this drug
to use by or on the order of a licensed veterinarian.

Federal law prohibits the extralabel use
of this drug in food-producing animals.

Each tablet contains: 68 mg enrofloxacin
Approved by FDA under ANADA # 200-680

50 Tablets

Dechra

PRINCIPAL DISPLAY PANEL - 136 mg Tablet Bottle Label

NDC: 17033-305-05

136 mg

Enroquin®

(enrofloxacin) Flavored Tablets
Antibacterial Tablets

136 mg

For The Treatment Of Susceptible
Bacterial Pathogens In Dogs And Cats

CAUTION: Federal (U.S.A.) law restricts this drug
to use by or on the order of a licensed veterinarian.

Federal law prohibits the extralabel use
of this drug in food-producing animals.

Each tablet contains: 136 mg enrofloxacin
Approved by FDA under ANADA # 200-680

50 Tablets

Dechra